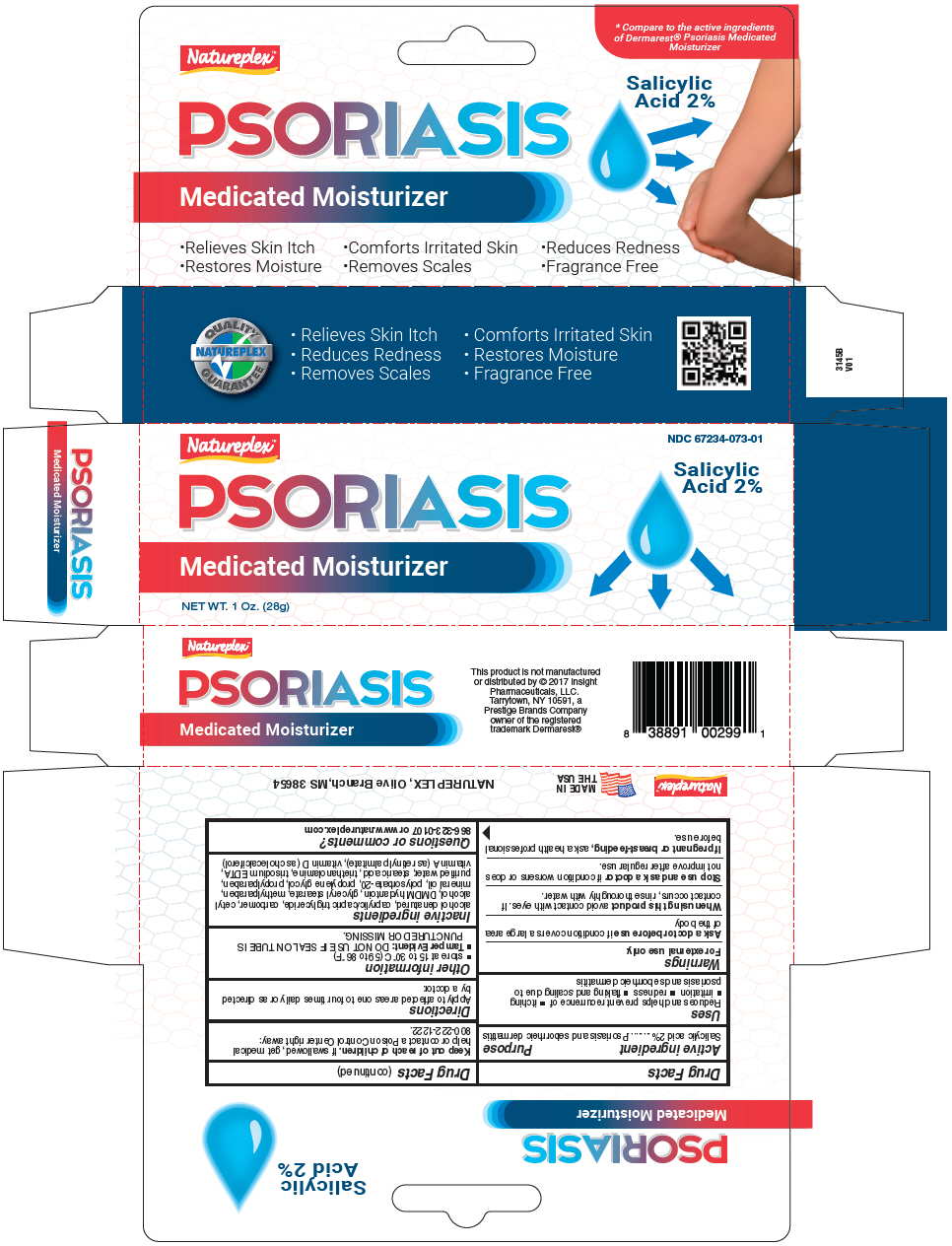 DRUG LABEL: NATUREPLEX PSORIASIS
NDC: 67234-073 | Form: CREAM
Manufacturer: Natureplex, LLC
Category: otc | Type: HUMAN OTC DRUG LABEL
Date: 20260129

ACTIVE INGREDIENTS: SALICYLIC ACID 20 mg/1 g
INACTIVE INGREDIENTS: ALCOHOL; MEDIUM-CHAIN TRIGLYCERIDES; CARBOMER HOMOPOLYMER, UNSPECIFIED TYPE; CETYL ALCOHOL; DMDM HYDANTOIN; GLYCERYL MONOSTEARATE; METHYLPARABEN; MINERAL OIL; POLYSORBATE 20; PROPYLENE GLYCOL; PROPYLPARABEN; WATER; STEARIC ACID; TROLAMINE; EDETATE TRISODIUM; VITAMIN A PALMITATE; CHOLECALCIFEROL

NATUREPLEX™ PSORIASIS

Drug Facts

Active ingredient

Salicylic acid 2%

Purpose

Psoriasis and seborrheic dermatitis

Uses

Reduces and helps prevent recurrence of

- itching
- irritation
- redness
- flaking and scaling due to psoriasis and seborrheic dermatitis

Warnings

For external use only.

Ask a doctor before use if condition covers a large area of the body

When using this product avoid contact with eyes. If contact occurs, rinse thoroughly with water.

Stop use and ask a doctor if condition worsens or does not improve after regular use.

PREGNANCY OR BREAST FEEDING

If pregnant or breast-feeding, ask a health professional before use.

Keep out of reach of children. If swallowed, get medical help or contact a Poison Control Center right away: 800-222-1222.

Directions

Apply to affected areas one to four times daily or as directed by a doctor.

Other information

- store at 15 to 30°C (59 to 86°F)
- Tamper Evident: DO NOT USE IF SEAL ON TUBE IS PUNCTURED OR MISSING.

Inactive ingredients

alcohol denatured, caprylic/capric triglyceride, carbomer, cetyl alcohol, DMDM hydantoin, glyceryl stearate, methylparaben, mineral oil, polysorbate-20, propylene glycol, propylparaben, purified water, stearic acid, triethanolamine, trisodium EDTA, vitamin A (as retinyl palmitate), vitamin D (as cholecalciferol)

Questions or comments?

866-323-0107 or www.natureplex.com

PRINCIPAL DISPLAY PANEL - 28 g Tube Carton

Natureplex™
PSORIASIS
Medicated Moisturizer

NET WT. 1 Oz. (28g)

NDC 67234-073-01

Salicylic
Acid 2%